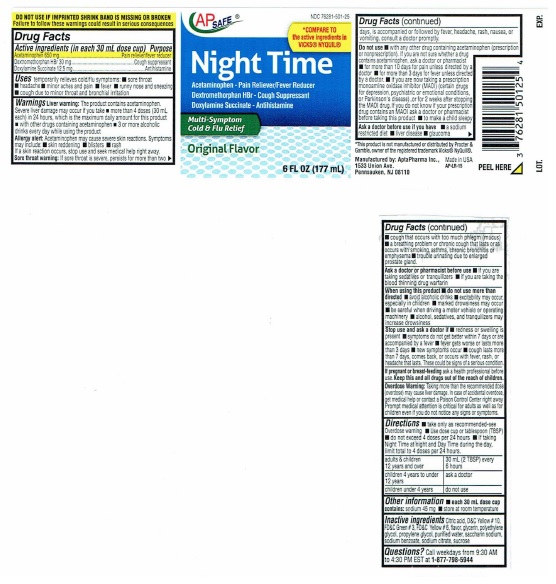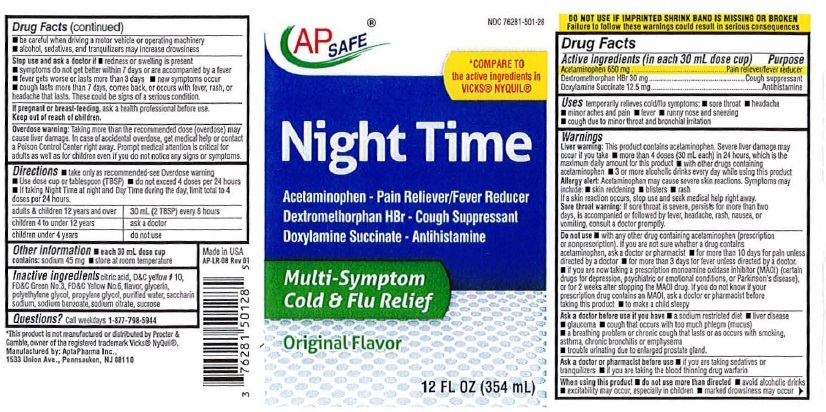 DRUG LABEL: Nite-Time

NDC: 76281-501 | Form: LIQUID
Manufacturer: AptaPharma Inc.
Category: otc | Type: HUMAN OTC DRUG LABEL
Date: 20251226

ACTIVE INGREDIENTS: ACETAMINOPHEN 650 mg/30 mL; DEXTROMETHORPHAN HYDROBROMIDE 30 mg/30 mL; DOXYLAMINE SUCCINATE 12.5 mg/30 mL
INACTIVE INGREDIENTS: CITRIC ACID MONOHYDRATE; D&C YELLOW NO. 10; FD&C GREEN NO. 3; FD&C YELLOW NO. 6; GLYCERIN; POLYETHYLENE GLYCOL 400; PROPYLENE GLYCOL; WATER; SACCHARIN SODIUM; SODIUM BENZOATE; SODIUM CITRATE; SUCROSE

Active Ingredients

Drug Facts

Active ingredients (in each 30 mL dose cup)

Acetaminophen 650 mg Dextromethorphan HBr 30 mg Doxylamine Succinate 12.5 mg

Purpose

Pain reliever/fever reducer Cough suppressant Antihistamine

Keep Out Of Reach Of Children

Uses

Uses temporarily relieves cold/flu symptoms:

- sore throat
- minor aches and pain
- runny nose and sneezing
- cough due to minor sore throat and bronchial irritation
- headache
- fever

Warnings

Liver warning:This product contains acetaminophen. Severe liver damage
may occur if you take ● more than 4 doses (30 mL each) in 24 hours, which is
the maximum daily amount for this product ● with other drugs containing
acetaminophen ● 3 or more alcoholic drinks everyday while using this product.

Sore throat warning:If sore throat is severe, persists for more than 2 days,

is accompanied or followed by fever, headache, rash, nausea, or vomiting, consult a doctor promptly.

Ask a doctor before use if you have

- a sodium restricted diet
- liver disease
- glaucoma
- cough that occurs with too much phlegm (mucus)
- a breathing problem or chronic cough that lasts or as occurs with smoking, asthma, chronic bronchitis or emphysema
- trouble urinating due to enlarged prostate gland

Ask a doctor or pharmacist before use

- if you are taking sedatives or tranquilizers
- if you are taking the blood thinning drug warfarin

When Using This Product

- do not use more than directed
- avoid alcoholic drinks
- excitability may occur, especially in children
- marked drowsiness may occur
- be careful when driving a motor vehicle or operating machinery
- alcohol, sedatives, and tranquilizers may increase drowsiness

Stop use and ask a doctor if

- redness or swelling is present
- symptoms do not get better within 7 days or are accompanied by a fever
- fever gets worse or lasts more than 3 days
- new symptoms occur
- cough lasts more than 7 days, comes back, or occurs with fever, rash, headache that lasts

Pregnant Or Breast-Feeding

If pregnant or breast-feeding, ask a health professional before use.

Overdose Warning

Overdose warning: Taking more than the recommended dose can cause serious health problems. In case of overdose, get medical help or contact a Poison Control Center right away. Quick medical attention is critical for adults as well as for children even if you do not notice any signs or symptoms.

Directions

- take only as recommended-see Overdose warnings
- Use dose cup or tablespoon (TBSP)
- do not exceed 4 doses per 24 hours

adults and children 12 years and over 30 mL (2TBSP) every 6 hours
children 4 to under 12 years ask a doctor
children under 4 years do not use

- If taking Nite Time at night and Day Time during the day, limit total to 4 doses per 24 hours

Other Information

- each 30 mL dose cup contains:

- sodium 45 mg
- store at room temperature

Inactive Ingredients

Inactive ingredients: citric acid, D and C yellow No. 10, FD and C Green No. 3, FD and C Yellow No. 6, flavor, glycerin, polyethylene glycol, propylene glycol, purified water, saccharin sodium, sodium benzoate, sodium citrate, sucrose

Do Not Use

- with any other drug containing acetaminophen (prescription or nonprescription) If you are not sure whether a drug contains acetaminophen, ask a doctor or pharmacist
- If you are now taking a prescription monoamine oxidase inhibitor (MAOI) (certain drugs for depression,psychiatric or emotional conditions, or Parkinson's disease), or for 2 weeks after stopping the MAOI drug. If you do not know if your prescription drug contains an MAOI, ask a doctor or pharmacist before taking this product
- to make a child sleepy

Package Label - Night Time Cold & Flu Relief

NDC 76281-501-28

AP SAFE

*COMPARE TO
the active ingredients in
VICKS®NYQUIL®

Night Time

Acetaminophen – Pain Reliever/Fever Reducer
Dextromethorphan HBr – Cough Suppressant
Doxylamine Succinate – Antihistamine

Multi-Symptom
Cold & Flu Relief

Original Flavor

12 FL OZ (354 mL)

DO NOT USE IF IMPRINTED SHRINK BAND IS MISSING OR BROKEN

Failure to follow these warnings could result in serious consequences

*This product is not manufactured or distributed by Procter &
Gamble, owner of the registered trademark Vicks® NyQuil®.

Manufactured by: AptaPharma Inc.,
1533 Union Ave., Pennsauken, NJ 08110

12 OZ

6 OZ

res